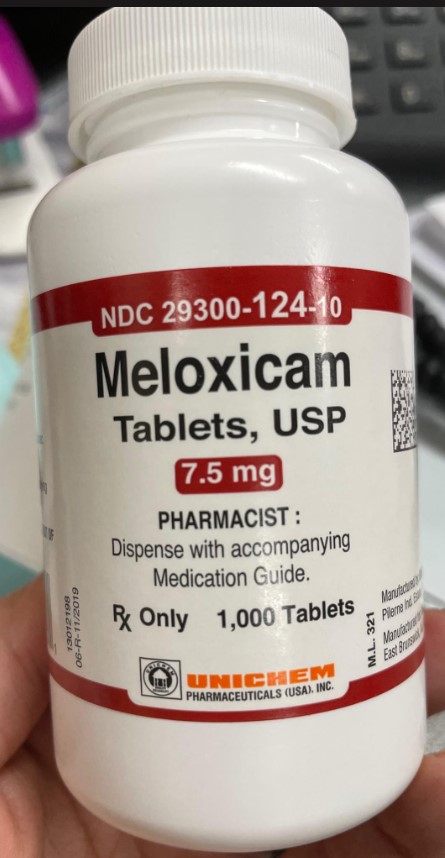 DRUG LABEL: Meloxicam
NDC: 80175-0124 | Form: TABLET
Manufacturer: Central Packaging
Category: prescription | Type: HUMAN PRESCRIPTION DRUG LABEL
Date: 20210305

ACTIVE INGREDIENTS: MELOXICAM 7.5 mg/1 1

INDICATIONS AND USAGE

Juvenile idiopathic arthritis

Relief of the signs and symptoms of pauciarticular or polyarticular course juvenile idiopathic arthritis in patients 2 years and older (suspension) and in pediatric patients weighing at least 60 kg (orally-disintegrating tablet).

Osteoarthritis

Relief of the signs and symptoms of osteoarthritis (OA); management of OA pain.

Rheumatoid arthritis (orally-disintegrating tablet, tablet, and suspension only)

Relief of the signs and symptoms of rheumatoid arthritis.

Medication Guide for Nonsteroidal Anti-inflammatory Drugs (NSAIDs)
What is the most important information I should know about medicines called Nonsteroidal Anti-inflammatory Drugs (NSAIDs)?
NSAIDs can cause serious side effects, including:
• Increased risk of a heart attack or stroke that can lead to death . This risk may happen early in treatment and may increase:
o with increasing doses of NSAIDs
o with longer use of NSAIDs
• Do not take NSAIDs right before or after a heart surgery called a "coronary artery bypass graft (CABG)."
• Avoid taking NSAIDs after a recent heart attack, unless your healthcare provider tells you to. You may have an increased risk of another heart attack if you take NSAIDs after a recent heart attack.
• Increased risk of bleeding, ulcers, and tears (perforation) of the esophagus (tube leading from the mouth to the stomach), stomach and intestines:
o anytime during use
o without warning symptoms
o that may cause death
The risk of getting an ulcer or bleeding increases with:
o past history of stomach ulcers, or stomach or intestinal bleeding with use of NSAIDs
o taking medicines called "corticosteroids", "anticoagulants", "SSRIs", or "SNRIs"
o increasing doses of NSAIDs
o longer use of NSAIDs
o smoking
o drinking alcohol
o older age
o poor health
o advanced liver disease
o bleeding problems
NSAIDs should only be used:
o exactly as prescribed
o at the lowest dose possible for your treatment
o for the shortest time needed
What are NSAIDs?
NSAIDs are used to treat pain and redness, swelling, and heat (inflammation) from medical conditions such as different types of arthritis, menstrual cramps, and other types of short-term pain.
Who should not take NSAIDs?
Do not take NSAIDs:
• if you have had an asthma attack, hives, or other allergic reaction with aspirin or any other NSAIDs.
• right before or after heart bypass surgery.
Before taking NSAIDs, tell your healthcare provider about all of your medical conditions, including if you:
• have liver or kidney problems
• have high blood pressure
• have asthma
• are pregnant or plan to become pregnant. Talk to your healthcare provider if you are considering taking NSAIDs during pregnancy. You should not take NSAIDs after 29 weeks of pregnancy.
• are breastfeeding or plan to breast feed.
Tell your healthcare provider about all of the medicines you take, including prescription or over-the-counter medicines, vitamins or herbal supplements. NSAIDs and some other medicines can interact with each other and cause serious side effects. Do not start taking any new medicine without talking to your healthcare provider first.
What are the possible side effects of NSAIDs?
NSAIDs can cause serious side effects, including:
See "What is the most important information I should know about medicines called Nonsteroidal Anti-inflammatory Drugs (NSAIDs)?"
• new or worse high blood pressure
• heart failure
• liver problems including liver failure
• kidney problems including kidney failure
• low red blood cells (anemia)
• life-threatening skin reactions
• life-threatening allergic reactions
• Other side effects of NSAIDs include: stomach pain, constipation, diarrhea, gas, heartburn, nausea, vomiting, and dizziness.
Get emergency help right away if you get any of the following symptoms:
• shortness of breath or trouble breathing
• chest pain
• weakness in one part or side of your body
• slurred speech
• swelling of the face or throat
Stop taking your NSAID and call your healthcare provider right away if you get any of the following symptoms:
• Nausea
• more tired or weaker than usual
• diarrhea
• itching
• your skin or eyes look yellow
• indigestion or stomach pain
• flu-like symptoms
• vomit blood
• there is blood in your bowel movement or it is black and sticky like tar
• unusual weight gain
• skin rash or blisters with fever
• swelling of the arms, legs, hands and feet
If you take too much of your NSAID, call your healthcare provider or get medical help right away.
These are not all the possible side effects of NSAIDs. For more information, ask your healthcare provider or pharmacist about NSAIDs.
Call your doctor for medical advice about side effects. You may report side effects to FDA at 1-800-FDA-1088.
Other information about NSAIDs:
• Aspirin is an NSAID but it does not increase the chance of a heart attack. Aspirin can cause bleeding in the brain, stomach, and intestines. Aspirin can also cause ulcers in the stomach and intestines.
• Some NSAIDs are sold in lower doses without a prescription (over-the-counter). Talk to your healthcare provider before using over-the-counter NSAIDs for more than 10 days.
General information about the safe and effective use of NSAIDs
Medicines are sometimes prescribed for purposes other than those listed in a Medication Guide. Do not use NSAIDs for a condition for which it was not prescribed. Do not give NSAIDs to other people, even if they have the same symptoms that you have. It may harm them.
If you would like more information about NSAIDs, talk with your healthcare provider. You can ask your pharmacist or healthcare provider for information about NSAIDs that is written for health professionals.
Additional Medication Guides can be obtained by calling Unichem at 1-866-562-4616.
The other trademarks referenced are owned by third parties not affiliated with Unichem Laboratories Limited
Manufactured by:
UNICHEM LABORATORIES LTD.
Pilerne Ind. Estate,
Pilerne, Bardez, Goa 403511, India
Manufactured for:
East Brunswick, NJ 08816
08-R-11/2020
13012881